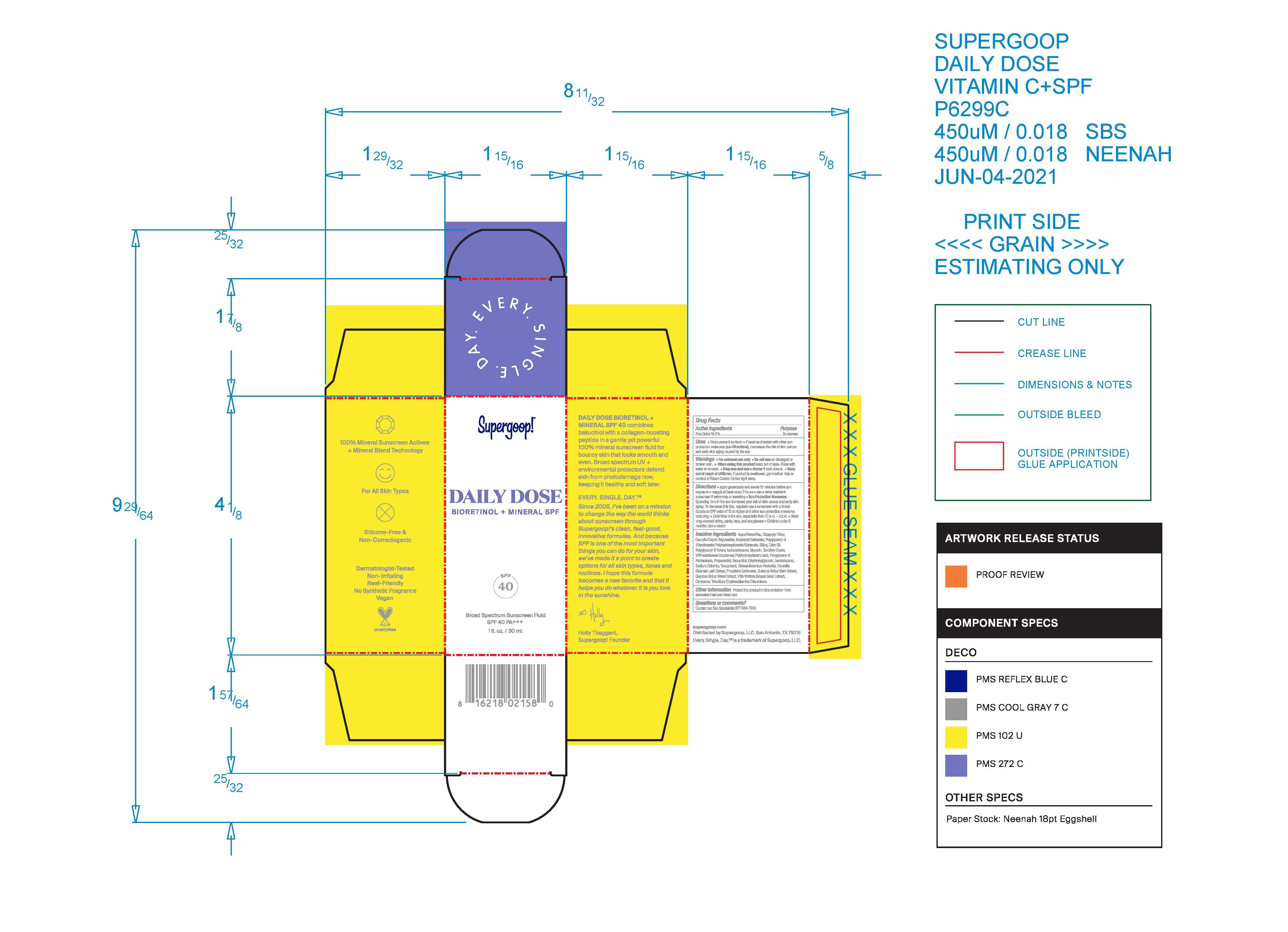 DRUG LABEL: DAILY SUPERGOOP DOSE BIORETINOL MINERAL SPF 40
NDC: 59735-614 | Form: LOTION
Manufacturer: MANA Products, INC
Category: otc | Type: HUMAN OTC DRUG LABEL
Date: 20240103

ACTIVE INGREDIENTS: ZINC OXIDE 16.5 g/100 mL
INACTIVE INGREDIENTS: TOCOPHEROL; PROPYLENE CARBONATE; PEG-6 SORBITAN OLEATE; SODIUM CHLORIDE; ETHYLHEXYLGLYCERIN; VITIS VINIFERA SEED; PROPANEDIOL; BAKUCHIOL; QUERCUS ROBUR TWIG BARK; CAMELLIA SINENSIS FLOWER; OLIVE OIL POLYGLYCERYL-6 ESTERS; VINYLPYRROLIDONE/HEXADECENE COPOLYMER; DISTEARDIMONIUM HECTORITE; POLYGLYCERYL-6 DIOLEATE; ISODODECANE; BUTYLOCTYL SALICYLATE; QUERCUS ROBUR WOOD; ISOHEXADECANE; DICAPRYLYL ETHER; POLYGLYCERYL-4 DIISOSTEARATE/POLYHYDROXYSTEARATE/SEBACATE; WATER; SILICON DIOXIDE; POLYHYDROXYSTEARIC ACID (2300 MW); GLYCERIN; TRISODIUM ETHYLENEDIAMINE DISUCCINATE; CARNOSINE; MEDIUM-CHAIN TRIGLYCERIDES

SUPERGOOP DAILY DOSE BIORETINOL MINERAL SPF 40

Active Ingredients

Zinc Oxide 16.5%

Purpose

Sunscreen

USES

Helps prevent sunburn
If used as directed with other sun protection measures (see Directions), decreases the
risk of Skin cancer and early skin aging caused by the sun

Warnings

For External use only
Do not use on damaged or broken skin
When using this product, Keep our of eyes. Rinse with water to remove. Stop use and ask a doctor if rash occurs.

Keep out of the Reach of Children

Keep our of reach of children. If product is swallowed, get medical help or contact a
Poison Control Center right away

Directions

• apply generously and evenly 15 minutes before sun exposure
• reapply at least every 2 hours
• use a water resistant sunscreen if swimming or sweating
Sun Protection Measures: Spending time in the sun increases your risk of skin
cancer and early skin aging. To decrease this risk, regularly use a sunscreen with a
Broad Spectrum SPF value of 15 or higher and other sun protection measures including:
◦ Limit time in the sun, especially from 10 a.m. - 2 p.m. ◦ Wear long-sleeved shirts,
pants, hats, and sunglasses • Children under 6 months: Ask a doctor

Inactive Ingredients

Aqua/Water/Eau, Dicaprylyl Ether, Caprylic/Capric Triglyceride, Butyloctyl Salicylate,
Polyglyceryl-4 Diisostearate/Polyhydroxystearate/Sebacate, Silica, Olive Oil Polyglyceryl-6
Esters, Isohexadecane, Glycerin, Sorbitan Oleate, VP/Hexadecene Copolymer,
Polyhydroxystearic acid, Polyglyceryl-6 Pentaoleate, Propanediol, Bakuchiol,
Ethylhexylglycerin, Isododecane, Sodium Chloride, Tocopherol, Disteardimonium
Hectorite, Camellia Sinensis Leaf Extract, Propylene Carbonate, Quercus Robur Bark
Extract, Quercus Robur Wood Extract, Vitis Vinifera (Grape) Seed Extract, Carnosine,
Trisodium Ethylenediamine Disuccinate

Other Information

Protect the product in this container from excessive heat and direct sun